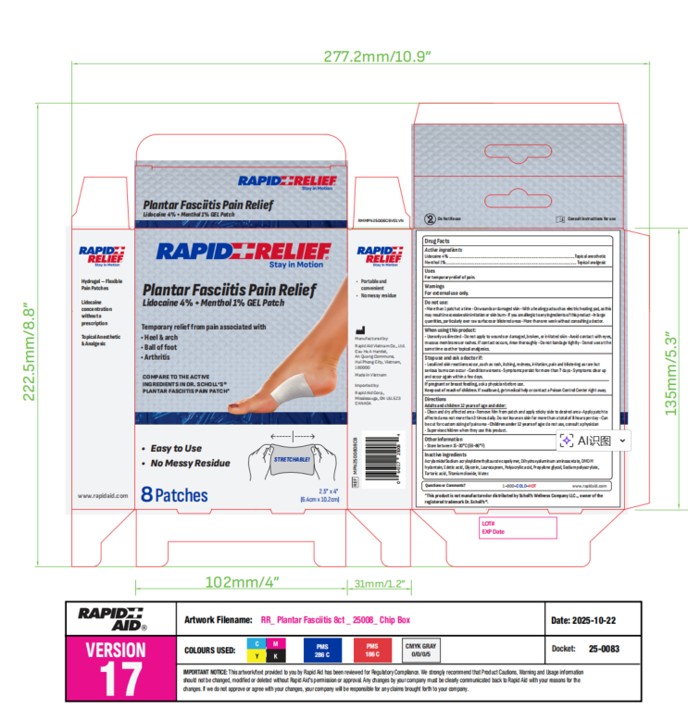 DRUG LABEL: Rapid Relief
NDC: 83569-014 | Form: PATCH
Manufacturer: RAPID AID VIET NAM COMPANY LIMITED
Category: otc | Type: HUMAN OTC DRUG LABEL
Date: 20251113

ACTIVE INGREDIENTS: MENTHOL 1 g/100 g; LIDOCAINE 4 g/100 g
INACTIVE INGREDIENTS: SODIUM POLYACRYLATE (8000 MW); DIHYDROXYALUMINUM AMINOACETATE; LAUROCAPRAM; ACRYLAMIDE/SODIUM ACRYLOYLDIMETHYLTAURATE COPOLYMER (120000 MPA.S AT 1%); TARTARIC ACID; PROPYLENE GLYCOL; TITANIUM DIOXIDE; POLYACRYLIC ACID (300000 MW); POLYACRYLIC ACID (800000 MW); GLYCERIN; WATER; DMDM HYDANTOIN; EDETATE DISODIUM ANHYDROUS

Active Ingredient(s)

Lidocaine 4 % +Menthol 1% w/w.

Purpose

Topical anesthetic

USE

For temporary relief of pain.

Warnings

For external use only.

Do not use

More than 1 patch at a time
On wounds or damaged skin
With a heating pad such as electric heating pad,as this may result in excessive skin irritation or skin burn
If you are allergic to any ingredients of this product
In large quantities, particularly over raw surfaces or blistered areas

More than one week without consulting a doctor.

When using this product:

Use only as directed

Do not apply to wounds or damaged, broken, or irritated skin

Avoid contact with eyes, mucous membranes or rashes.If contact occurs, rinse thoroughly

Do not bandage tightly

Do not use at the same time as other topical analgesics.

Stop use and ask a doctor if:

Localized skin reactions occur, such as rash, itching, redness, irritation, pain and blistering as rare but serious burns can occur

Condition worsens

Symptoms persist for more than 7 days

Symptoms clear up and occur again within a few days

If pregnant or breastfeeding, ask a physicianbefore use.

Keep out of reach of children. If swallowed, get medical help or contact a Poison Control Center right away.

Directions

Adults and children 12 years of age and older:

Clean and dry affected area

Remove film from patch and apply sticky side to desired area

Apply patch to affected area not more than 3 times daily

Do not leave on skin for more than a total of 8 hours per day

Can be cut for custom sizing of pain area

Children under 12 years of age:

Do not use, consult a doctor

Supervise children when they use this product

STORAGE AND HANDLING

Store between 15-30℃(59-86℉）

Inactive ingredients

Acrylamide/Sodium acryloyldimethyltaurate copolymer, Dihydroxyaluminum aminoacetate,DMDM

hydantoin, Edetic acid, Glycerin, Laurocapram, Polyacrylic acid, Propylene glycol,Sodium polyacrylate,

Tartaric acid, Titanium dioxide,Water.